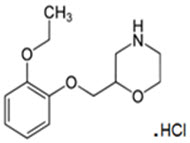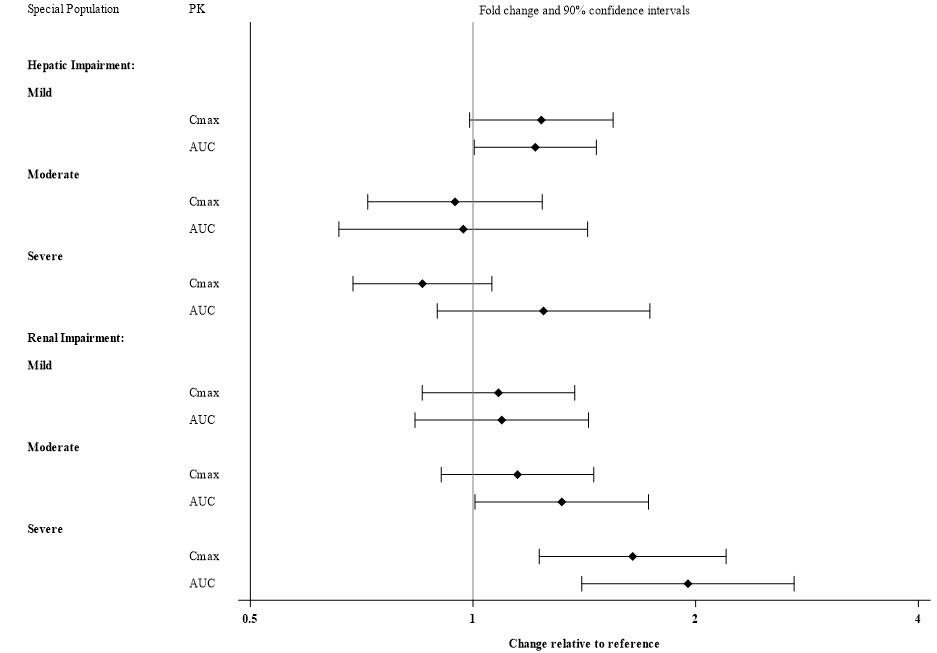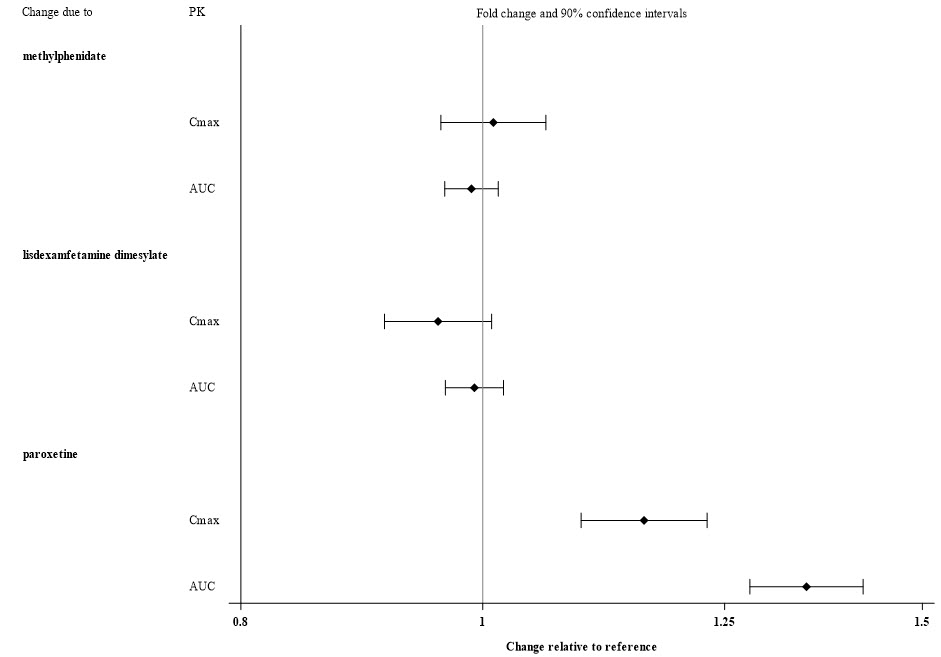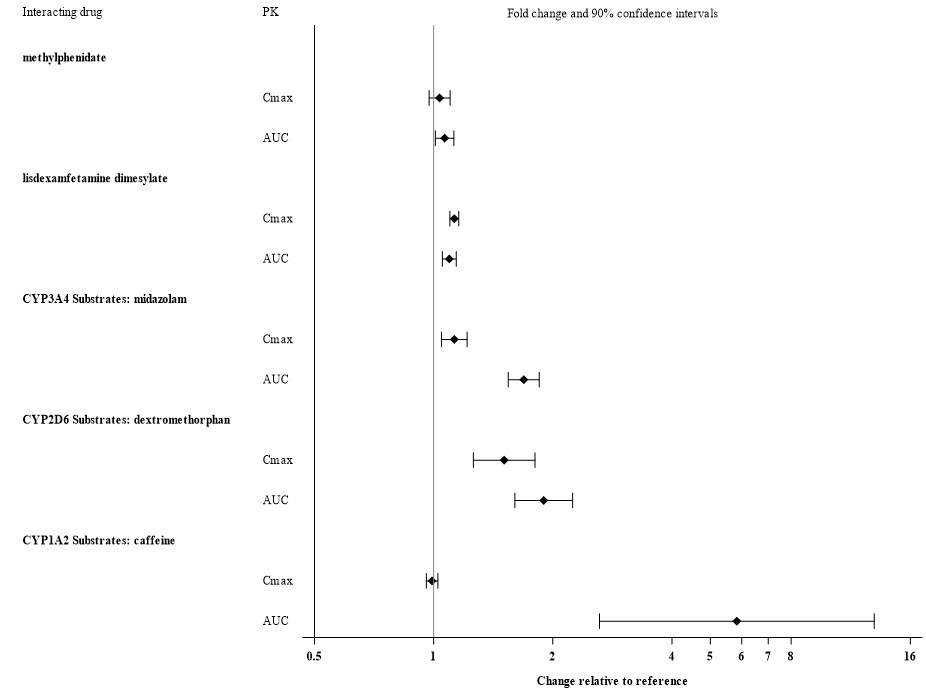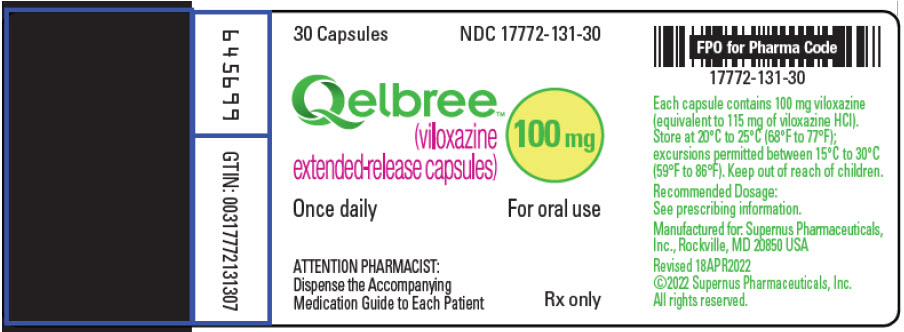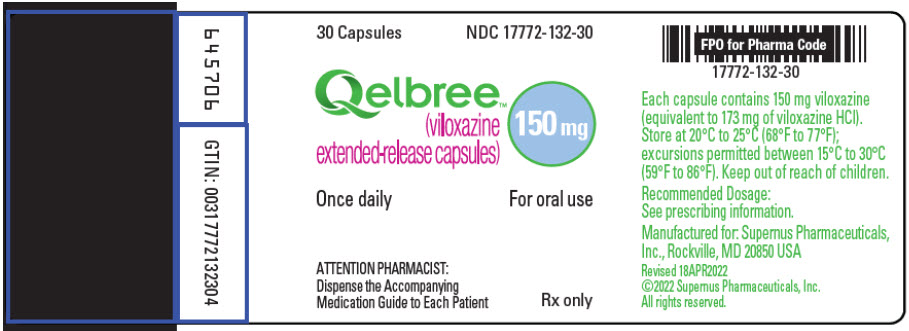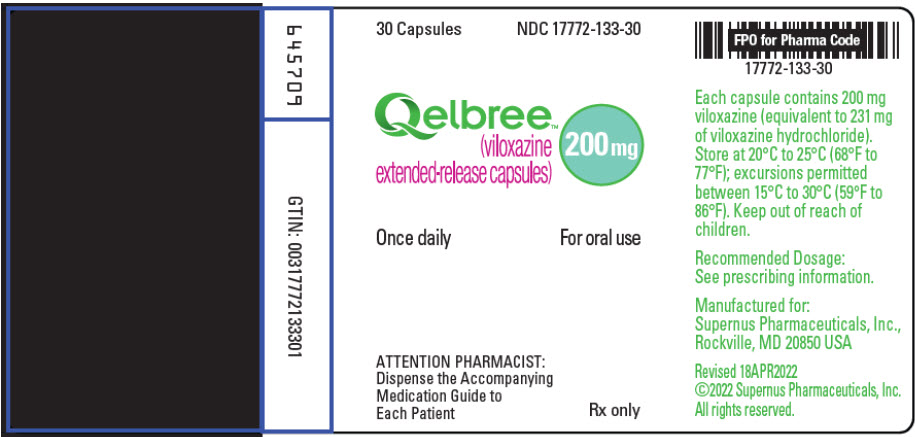 DRUG LABEL: QELBREE
NDC: 17772-131 | Form: CAPSULE, EXTENDED RELEASE
Manufacturer: Supernus Pharmaceuticals, Inc
Category: prescription | Type: HUMAN PRESCRIPTION DRUG LABEL
Date: 20251205

ACTIVE INGREDIENTS: VILOXAZINE HYDROCHLORIDE 100 mg/1 1
INACTIVE INGREDIENTS: SUCROSE; STARCH, CORN; HYPROMELLOSE 2910 (5 MPA.S); TRIACETIN; POLYETHYLENE GLYCOL 3350; LACTOSE MONOHYDRATE; TITANIUM DIOXIDE; ETHYLCELLULOSE, UNSPECIFIED; WATER; AMMONIA; MEDIUM-CHAIN TRIGLYCERIDES; OLEIC ACID; TALC; D&C YELLOW NO. 10; FD&C YELLOW NO. 6; GELATIN, UNSPECIFIED; SHELLAC; ALCOHOL; ISOPROPYL ALCOHOL; BUTYL ALCOHOL; PROPYLENE GLYCOL; FERROSOFERRIC OXIDE; POTASSIUM HYDROXIDE

HIGHLIGHTS OF PRESCRIBING INFORMATION

These highlights do not include all the information needed to use QELBREE® safely and effectively. See full prescribing information for QELBREE®.
QELBREE® (viloxazine extended-release capsules), for oral use
Initial U.S. Approval: 2021

WARNING: SUICIDAL THOUGHTS AND BEHAVIORS

See full prescribing information for complete boxed warning.

In clinical trials, higher rates of suicidal thoughts and behavior were reported in patients treated with Qelbree than in patients treated with placebo. Closely monitor for worsening and emergence of suicidal thoughts and behaviors (5.1).

1 INDICATIONS AND USAGE

Qelbree is a selective norepinephrine reuptake inhibitor indicated for the treatment of Attention Deficit Hyperactivity Disorder (ADHD) in adults and pediatric patients 6 years and older (1)

2 DOSAGE AND ADMINISTRATION

- Pediatric patients 6 to 11 years of age: Recommended starting dosage is 100 mg once daily. May titrate in increments of 100 mg weekly to the maximum recommended dosage of 400 mg once daily (2.2)
- Pediatric patients 12 to 17 years of age: Recommended starting dosage is 200 mg once daily. May titrate after 1 week, by an increment of 200mg, to the maximum recommended dosage of 400 mg once daily (2.2)
- Adult patients: Recommended starting dosage is 200 mg once daily. May titrate in increments of 200 mg weekly, to maximum recommended dosage of 600 mg once daily (2.2)
- Capsules may be swallowed whole or opened and the entire contents sprinkled onto applesauce or pudding (2.3)
- Severe Renal Impairment :Initial dosage is 100 mg once daily. Titrate in weekly increments of 50 mg to 100 mg to a maximum recommended dosage of 200 mg once daily (2.4, 8.6)

3 DOSAGE FORMS AND STRENGTHS

Extended-release capsules: 100 mg, 150 mg and 200 mg (3)

4 CONTRAINDICATIONS

- Concomitant administration of monoamine oxidase inhibitors (MAOI), or dosing within 14 days after discontinuing an MAOI (4, 7.1)
- Concomitant administration of sensitive CYP1A2 substrates or CYP1A2 substrates with a narrow therapeutic range (4, 7.1)

5 WARNINGS AND PRECAUTIONS

- Blood Pressure and Heart Rate Increases: Assess heart rate and blood pressure prior to initiating treatment, following increases in dosage, and periodically while on therapy (5.2)
- Activation of Mania or Hypomania: Screen patients for bipolar disorder (5.3)
- Somnolence and Fatigue: Advise patients to use caution when driving or operating hazardous machinery due to potential somnolence (including sedation and lethargy) and fatigue (5.4)

6 ADVERSE REACTIONS

Most commonly observed adverse reactions (≥5% and at least twice the rate of placebo) were:

Pediatric patients 6 to 17 years of age: somnolence, decreased appetite, fatigue, nausea, vomiting, insomnia, and irritability (6.1)

Adult patients: insomnia, headache, somnolence, fatigue, nausea, decreased appetite, dry mouth and constipation (6.1)

To report SUSPECTED ADVERSE REACTIONS, contact Supernus Pharmaceuticals at 1-866-398-0833 or FDA at 1-800-FDA-1088 or www.fda.gov/medwatch.

7 DRUG INTERACTIONS

Moderate sensitive CYP1A2 substrates: Not recommended for coadministration with Qelbree. Dose reduction may be warranted (7.1)

8 USE IN SPECIFIC POPULATIONS

- Pregnancy :May cause maternal harm; discontinue when pregnancy is recognized (8.1)

FULL PRESCRIBING INFORMATION

WARNING: SUICIDAL THOUGHTS AND BEHAVIORS

In clinical studies, higher rates of suicidal thoughts and behavior were reported in patients with ADHD treated with Qelbree than in patients treated with placebo. Closely monitor all Qelbree-treated patients for clinical worsening, and for emergence of suicidal thoughts and behaviors [see Warnings and Precautions (5.1)] .

1 INDICATIONS AND USAGE

Qelbree is indicated for the treatment of Attention-Deficit Hyperactivity Disorder (ADHD) in adults and pediatric patients 6 years and older.

2 DOSAGE AND ADMINISTRATION

2.1 Important Considerations Prior to Initiating Treatment

- Assess heart rate and blood pressure prior to initiating treatment with Qelbree, following increases in dosage, and periodically while on therapy [see Warnings and Precautions (5.2)] .
- Prior to initiating treatment with Qelbree, screen patients for a personal or family history of suicide, bipolar disorder, and depression [see Warnings and Precautions (5.3)].

2.2 Recommended Dosage

Pediatric patients

The recommended starting dosage for pediatric patients 6 to 11 years of age is 100 mg orally once daily. Dosage may be titrated in increments of 100 mg at weekly intervals to the maximum recommended dosage of 400 mg once daily, depending on response and tolerability.

The recommended starting dosage for pediatric patients 12 to 17 years of age is 200 mg orally once daily. After 1 week, dosage may be titrated by an increment of 200 mg to the maximum recommended dosage of 400 mg once daily, depending on response and tolerability.

Adult patients

The recommended starting dosage for adults is 200 mg orally once daily. Dosage may be titrated in increments of 200 mg weekly to the maximum recommended dosage of 600 mg once daily, depending on response and tolerability.

Pharmacological treatment of ADHD may be needed for extended periods. Periodically reevaluate the long-term use of Qelbree and adjust dosage as needed.

2.3 Administration Information

Administer Qelbree orally with or without food [see Clinical Pharmacology (12.3)] . Do not cut, crush, or chew the capsules.

Swallow Qelbree capsules whole, or open the capsule and sprinkle the entire contents over a teaspoonful or tablespoonful of pudding or applesauce. Consume the food mixture in its entirety, without chewing, within 15 minutes for pudding, or within 2 hours for applesauce; do not store for future use.

2.4 Dosage Recommendations in Patients with Renal Impairment

In patients with severe renal impairment (eGFR < 30 mL/min/1.73m^2), the recommended starting dosage is 100 mg once daily. Dosage may be titrated in weekly increments of 50 to 100 mg once daily, to a maximum recommended dosage of 200 mg once daily.

No dosage adjustment is recommended in patients with mild to moderate (eGFR of 30 to 89 mL/min/1.73m^2) renal impairment [see Use in Specific Populations (8.6)] .

3 DOSAGE FORMS AND STRENGTHS

Qelbree (viloxazine extended-release capsules) are available as:

100 mg: yellow opaque body and cap (printed "SPN" on the cap, "100" on the body)

150 mg: lavender opaque body and cap (printed "SPN" on the cap, "150" on the body)

200 mg: light green opaque body and cap (printed "SPN" on the cap, "200" on the body)

4 CONTRAINDICATIONS

Qelbree is contraindicated in patients:

- receiving concomitant treatment with monoamine oxidase inhibitors (MAOI), or within 14 days following discontinuing an MAOI, because of an increased risk of hypertensive crisis [see Drug Interactions (7.1)] .
- receiving concomitant administration of sensitive CYP1A2 substrates or CYP1A2 substrates with a narrow therapeutic range [see Drug Interactions (7.1)].

5 WARNINGS AND PRECAUTIONS

5.1 Suicidal Thoughts and Behaviors

Higher rates of suicidal thoughts and behaviors were reported in pediatric and adult patients with ADHD treated with Qelbree than in patients treated with placebo.

Among 1019 pediatric patients exposed to Qelbree 100 mg to 400 mg in short-term trials, a total of nine patients (0.9%) reported suicidal ideation (N=6), behavior (N=1) or both (N=2). Eight patients reported suicidal ideation or behavior on the Columbia Suicide Severity Rating Scale (C-SSRS), a validated scale that assesses suicide risk. An additional patient treated with Qelbree reported suicidal behavior during the clinical trials, but did not report it on the C-SSRS. Among 463 patients treated with placebo in these studies, two patients (0.4%) reported suicidal ideation on the C-SSRS. No patients treated with placebo reported suicidal behavior. No completed suicides occurred in these trials.

Among 189 adults treated with Qelbree, a total of three patients (1.6%) reported suicidal ideation on the C-SSRS, versus 0 of 183 adults treated with placebo. No adults treated with either Qelbree or placebo reported suicidal behavior on the C-SSRS in the study. No attempted or completed suicides occurred in the trial.

Patients treated with Qelbree had higher rates of insomnia and irritability [see Adverse Reactions (6.1)] . Although a causal link between the emergence of insomnia and irritability and the emergence of suicidal impulses has not been established, there is a concern that these and other symptoms such as depressed mood, anxiety, agitation, akathisia, mania, hypomania, panic attacks, impulsive behavior, and aggression may represent precursors to emerging suicidal ideation or behavior. Thus, patients being treated with Qelbree should be observed for the emergence of precursor symptoms.

Closely monitor all Qelbree-treated patients for clinical worsening and emergence of suicidal thoughts and behaviors, especially during the initial few months of drug therapy, and at times of dosage changes. Consider changing the therapeutic regimen, including possibly discontinuing Qelbree, in patients who are experiencing emergent suicidal thoughts and behaviors or symptoms that might be precursors to emerging suicidal ideation or behavior, especially if these symptoms are severe or abrupt in onset, or were not part of the patient's presenting symptoms. Advise family members or caregivers of patients to monitor for the emergence of suicidal ideation or behavior, and to report such symptoms immediately to the healthcare provider.

5.2 Blood Pressure and Heart Rate Increases

Qelbree can cause an increase in heart rate and diastolic blood pressure.

Pediatric Patients

In a clinical study in pediatric patients 6 to 11 years of age, 34/154 (22%) of patients treated with Qelbree 100 mg daily had a ≥20 beat per minute (bpm) increase in heart rate at any time point in the clinical trial, compared to 15/159 (9%) of patients who received placebo. This finding was observed in 84/268 (31%) who received the 200 mg daily dosage, compared to 39/262 (15%) of patients in the placebo group, and in 28/100 (28%) of patients who received the 400 mg daily dosage, compared to 24/103 (23%) of patients who received placebo.

In a clinical study in pediatric patients 12 to 17 years of age, 22/99 (22%) of patients treated with Qelbree 200 mg daily had a ≥20 bpm increase in heart rate at any time point in the clinical trial, compared to 15/104 (14%) of patients who received placebo. This finding was observed in 69/205 (34%) who received the 400 mg daily dosage, compared to 35/201 (17%) of patients in the placebo group. In pediatric patients 12 to 17 years of age, 52/205 (25%) of patients treated with Qelbree 400 mg daily had a ≥ 15 mmHg increase in diastolic blood pressure at any time in the clinical trial, compared to 26/201 (13%) of patients in the placebo group.

Adult Patients

In a clinical study in adult patients (18 to 60 years of age), 52/178 (29%) of patients treated daily with Qelbree (200 mg to 600 mg) had a ≥20 beat per minute (bpm) increase in heart rate at any time point in the clinical trial, compared to 23/181 (13%) of patients who received placebo. Of patients treated daily with Qelbree (200 to 600 mg), 23/178 (13%) had a ≥ 15 mmHg increase in diastolic blood pressure at any time in the clinical trial, compared to 16/181 (9%) of patients in the placebo group.

Assess heart rate and blood pressure prior to initiating treatment with Qelbree, following increases in dosage, and periodically while on therapy [see Dosage and Administration (2.1)] .

5.3 Activation of Mania or Hypomania

Noradrenergic drugs, such as Qelbree, may induce a manic or mixed episode in patients with bipolar disorder. Prior to initiating treatment with Qelbree, screen patients to determine if they are at risk for bipolar disorder; such screening should include a detailed psychiatric history, including a personal or family history of suicide, bipolar disorder, and depression [see Dosage and Administration (2.1)].

5.4 Somnolence and Fatigue

Qelbree can cause somnolence and fatigue. In the short-term, placebo-controlled clinical trials in pediatric patients (6 to 17 years) with ADHD, somnolence (including lethargy and sedation) was reported in 16% of Qelbree-treated patients compared to 4% of placebo-treated patients. Fatigue was reported in 6% of Qelbree-treated patients, compared to 2% of placebo-treated patients [see Adverse Reactions (6.1)]. In adults, somnolence was reported in 6% of Qelbree-treated patients versus 2% in placebo-treated patients. Fatigue was reported in 12% of Qelbree-treated patients versus 3% of placebo-treated patients.

Patients should not perform activities requiring mental alertness, such as operating a motor vehicle or operating hazardous machinery until they know how they will be affected by Qelbree.

6 ADVERSE REACTIONS

The following serious adverse reactions are described in other sections of the labeling:

- Suicidal Thoughts and Behaviors [see Warnings and Precautions (5.1)]
- Blood Pressure and Heart Rate Increases [see Warnings and Precautions (5.2)]
- Activation of Mania or Hypomania [see Warnings and Precautions (5.3)]
- Somnolence and Fatigue [see Warnings and Precautions (5.4)]

6.1 Clinical Trials Experience

Because clinical trials are conducted under widely varying conditions, adverse reaction rates observed in the clinical trials of a drug cannot be directly compared to rates in the clinical trials of another drug and may not reflect the rates observed in practice.

The safety of Qelbree has been evaluated in 1118 pediatric patients (6 to 17 years of age) with ADHD exposed to one or more doses in short-term (6 to 8 week), randomized, double-blind, placebo-controlled trials. A total of 682 pediatric patients 6 to 17 years of age were treated for at least 6 months, and 347 pediatric patients 6 to 17 years of age for at least 12 months with Qelbree.

The safety of Qelbree has been evaluated in 189 adult patients (18 to 60 years of age) with ADHD exposed to one or more doses in a short-term (6 week), randomized, double-blind, placebo-controlled trial. A total of 277 adult patients with ADHD have been exposed to one or more doses of Qelbree. Eighty-four adult patients were treated for at least 6 months, and 22 adult patients for at least 12 months.

Pediatric Patients (6 to 17 Years of Age)

The data described below reflect exposure to Qelbree in 826 pediatric patients (6 to 17 years) who participated in randomized, double-blind, placebo-controlled trials with doses ranging from 100 mg to 400 mg. The population (N=826) was 65% male, 35% female, 54% White, 41% Black, 4% multiracial, and 1% other races.

Adverse Reactions Leading to Discontinuation of Qelbree Treatment: Approximately 3% (n=27) of the 826 patients receiving Qelbree in clinical studies discontinued treatment due to an adverse reaction. The adverse reactions most commonly associated with discontinuation of Qelbree were somnolence (n=5), nausea (n=3), headache (n=2), irritability (n=2), tachycardia (n=2), fatigue (n=2), and decreased appetite (n=2).

Most Common Adverse Reactions (occurring at ≥5% and at least twice the placebo rate for any dose): somnolence, decreased appetite, fatigue, nausea, vomiting, insomnia, and irritability.

Table 1 lists adverse reactions that occurred in at least 2% of patients treated with Qelbree and more frequently in Qelbree-treated patients than in placebo-treated patients. Table 1 data represents pooled data from pediatric patients 6 to 17 years of age who were enrolled in randomized, placebo-controlled trials of Qelbree.

Table 1. Adverse Reactions Reported in ≥2% of Pediatric Patients (6 to 17 Years of Age) Treated with Qelbree and at a Rate Greater than Placebo-Treated Patients in Placebo-Controlled ADHD Studies
 |  | Qelbree
Body System Adverse Reaction | Placebo N=463 (%) | 100mg N=154 (%) | 200mg N=367 (%) | 400mg N=305 (%) | All Qelbree N=826 (%)
Nervous system disorders
Somnolence [The following terms were combined: Somnolence: somnolence, lethargy, sedation Headache: headache, migraine, migraine with aura, tension headache Upper respiratory tract infection: nasopharyngitis, pharyngitis, sinusitis, upper respiratory tract infection, viral sinusitis, viral upper respiratory tract infection Abdominal pain: abdominal discomfort, abdominal pain, abdominal pain lower, abdominal pain upper Insomnia: initial insomnia, insomnia, middle insomnia, poor quality sleep, sleep disorder, terminal insomnia] | 4 | 12 | 16 | 19 | 16
Headache | 7 | 10 | 11 | 11 | 11
Metabolic and nutritional disorders
Decreased appetite | 0.4 | 5 | 8 | 8 | 7
Infections and infestations
Upper respiratory tract infection | 6 | 5 | 7 | 8 | 7
Body as a Whole - General disorders
Fatigue | 2 | 4 | 5 | 9 | 6
Pyrexia | 0.2 | 3 | 2 | 1 | 2
Gastrointestinal system disorders
Abdominal Pain | 4 | 3 | 6 | 7 | 5
Nausea | 3 | 1 | 4 | 7 | 5
Vomiting | 2 | 5 | 3 | 6 | 4
Psychiatric disorders
Insomnia | 1 | 2 | 5 | 5 | 4
Irritability | 1 | 3 | 2 | 5 | 3

Effects on Weight:In short–term, controlled studies (6 to 8 weeks), Qelbree-treated patients 6 to 11 years of age gained an average of 0.2 kg, compared to a gain of 1 kg in same-aged patients who received placebo. Qelbree-treated patients 12 to 17 years of age lost an average of 0.2 kg, compared to a weight gain of 1.5 kg in same-aged patients who received placebo. In a long-term open-label extension safety trial, 1097 patients received at least 1 dose of Qelbree. Among the 338 patients evaluated at 12 months, the mean change from baseline in weight-for-age z-score was -0.2 (standard deviation of 0.5). In the absence of a control group, it is unclear whether the weight change observed in the long-term open-label extension was attributable to the effect of Qelbree.

Adults

The data described below reflect exposure to Qelbree in 189 adults with ADHD who participated in the flexible-dose, randomized, double-blind, placebo-controlled trial with doses ranging from 200 mg to 600 mg. The population (N=189) was 56% male, 44% female, 81% White, 12% Black, 3% Asian, 3% other races and 1% multiracial.

Adverse Reactions Leading to Discontinuation of Qelbree Treatment: Approximately 9% of the 189 patients receiving Qelbree in clinical studies discontinued treatment due to an adverse reaction. The adverse reactions most commonly associated with discontinuation of Qelbree were fatigue (n=4), insomnia (n=3), constipation (n=3), and headache (n=2).

Most Common Adverse Reactions (occurring at ≥5% and at least twice the placebo rate of Qelbree):insomnia, headache, somnolence, fatigue, nausea, decreased appetite, dry mouth, and constipation.

Table 2 lists adverse reactions that occurred in at least 2% of patients treated with Qelbree and more frequently in Qelbree-treated patients than in placebo-treated patients. Table 2 represents data from adults with ADHD who were enrolled in a flexible-dose, randomized, placebo-controlled trial of Qelbree at doses of 200 mg to 600 mg.

Table 2. Adverse Reactions Reported in ≥2% of Adults Treated with Qelbree and at a Rate Greater than Placebo-Treated Patients in a Flexible-Dose Placebo-Controlled ADHD Study
Body System Adverse Reaction | Placebo N=183 (%) | Qelbree (200 mg to 600 mg) N=189 (%)
Psychiatric disorders
Insomnia [The following terms were combined: Somnolence: somnolence, lethargy, sedation Headache: headache, migraine, migraine with aura, tension headache Insomnia: initial insomnia, insomnia, middle insomnia, poor quality sleep, sleep disorder, terminal insomnia] | 7 | 23
Irritability | 3 | 4
Nervous system disorders
Headache | 7 | 17
Somnolence | 2 | 6
Dizziness | 2 | 4
Gastrointestinal system disorders
Nausea | 3 | 12
Dry mouth | 2 | 10
Constipation | 1 | 6
Vomiting | 1 | 4
Gastrooesophageal reflux disease | 1 | 2
Body as a Whole - General disorders
Fatigue | 3 | 12
Metabolic and nutritional disorders
Decreased appetite | 3 | 10
Cardiac Disorders
Tachycardia | 1 | 4

7 DRUG INTERACTIONS

7.1 Drugs Having Clinically Important Interactions with Qelbree

Table 3: Clinically Important Drug Interactions with Qelbree
Monoamine Oxidase Inhibitors (MAOI)
Clinical Impact | Concomitant use of Qelbree with an MAOI may lead to a potentially life-threatening hypertensive crisis.
Intervention | Concomitant use of Qelbree with an MAOI or within 2 weeks after discontinuing an MAOI is contraindicated [see Contraindications (4)] .
Sensitive CYP1A2 Substrates or CYP1A2 Substrates with a Narrow Therapeutic Range
Clinical Impact | Viloxazine is a strong CYP1A2 inhibitor. Concomitant use of viloxazine significantly increases the total exposure, but not peak exposure, of sensitive CYP1A2 substrates [see Clinical Pharmacology (12.3)] , which may increase the risk of adverse reactions associated with these CYP1A2 substrates.
Intervention | Coadministration with Qelbree is contraindicated [see Contraindications (4)] .
Moderate Sensitive CYP1A2 Substrate
Clinical Impact | Viloxazine is a strong CYP1A2 inhibitor. Concomitant use of viloxazine significantly increases the total, but not peak, exposure of sensitive CYP1A2 substrates [see Clinical Pharmacology (12.3)] , which may increase the risk of adverse reactions associated with these CYP1A2 substrates.
Intervention | Not recommended for coadministration with Qelbree. Dose reduction may be warranted if coadministered.
CYP2D6 Substrates
Clinical Impact | Viloxazine is a weak inhibitor of CYP2D6, and increases the exposure of CYP2D6 substrates when coadministered [see Clinical Pharmacology (12.3)] .
Intervention | Monitor patients for adverse reactions and adjust dosages of CYP2D6 substrates, as clinically indicated.
CYP3A4 Substrates
Clinical Impact | Viloxazine is a weak inhibitor of CYP3A4 which increases the exposure of CYP3A4 substrates when coadministered [see Clinical Pharmacology (12.3)].
Intervention | Monitor patients for adverse reactions and adjust dosages of CYP3A4 substrates, as clinically indicated.

8 USE IN SPECIFIC POPULATIONS

8.1 Pregnancy

Pregnancy Exposure Registry

There is a pregnancy exposure registry that monitors pregnancy outcomes in women exposed Qelbree during pregnancy. Healthcare providers are encouraged to register patients by calling the National Pregnancy Registry for Psychiatric Medications at 1-866-961-2388 or visiting online at www.womensmentalhealth.org/preg.

Risk Summary

Based on findings from animal reproduction studies, viloxazine may cause maternal harm when used during pregnancy. Discontinue Qelbree when pregnancy is recognized unless the benefits of therapy outweigh the potential risk to the mother. Available data from case series with viloxazine use in pregnant women are insufficient to determine a drug-associated risk of major birth defects, miscarriage or adverse maternal outcomes.

In animal reproduction studies, oral administration of viloxazine during the period of organogenesis caused fetal toxicities and delayed fetal development in the rat and maternal toxicities in the rabbit at doses approximately equal to the maximum recommended human dose (MRHD) of 600 mg in adults, based on mg/m^2.Oral administration of viloxazine to pregnant rats and mice during pregnancy and lactation caused maternal toxicities and deaths and fetal toxicities at doses equal to or less than the MRHD of 600 mg in adults, based on mg/m^2, respectively (see Data).

The estimated background risk of major birth defects and miscarriage for the indicated population is unknown. All pregnancies have a background risk of birth defect, loss, or other adverse outcomes. In the U.S. general population, the estimated background risk of major birth defects and miscarriage in clinically recognized pregnancies is 2 to 4% and 15 to 20%, respectively.

Data

Animal Data

Viloxazine was administered orally to pregnant rats during the period of organogenesis at doses of 13, 33, and 82 mg/kg/day. The high dose is approximately equal to the MRHD of 600 mg in adults, based on mg/m^2. Viloxazine did not cause maternal toxicity up to the high dose. Viloxazine at the high dose increased early and late resorption, delayed fetal development, and possibly caused low incidences of fetal malformations or anomalies (craniorachischisis, missing cervical vertebrae, and morphological changes associated with hydranencephaly). The NOAEL for fetal toxicity and malformation is 33 mg/kg/day, which is less than the MRHD of 600 mg in adults, based on mg/m^2.

Viloxazine was administered orally to pregnant rabbits during the period of organogenesis at doses of 43, 87, and 130 mg/kg/day, which are approximately 1, 3, and 4 times the MRHD of 600 mg in adults, based on mg/m^2, respectively. Viloxazine decreased maternal body weight, weight gain, or food consumption at doses ≥ 87 mg/kg/day but did not cause fetal toxicity at doses up to 130 mg/kg/day. The NOAELs for maternal and fetal toxicity is 43 and 130 mg/kg/day, respectively, which is approximately 1 and 4 times the MRHD, based on mg/m^2, respectively.

Viloxazine was administered orally to pregnant rats during gestation and lactation at doses of 43, 87, and 217 mg/kg/day, which are less than, equal to , and 4 times the MRHD of 600 mg in adults, based on mg/m^2, respectively. Viloxazine caused maternal toxicity of decreased body weight, weight gain, and food consumption at doses ≥ 87 mg/kg/day and maternal deaths near term at 217 mg/kg/day. At these maternally toxic doses, viloxazine caused lower live birth, decreased viability, and delayed growth and sexual maturation without affecting learning and memory in the offspring. The NOAEL for maternal and developmental toxicity is 43 mg/kg/day, which is less than the MRHD of 600 mg in adults, based on mg/m^2.

Viloxazine was administered orally to pregnant mice during gestation and lactation at doses of 13, 33, and 82 mg/kg/day, which are less than the MRHD of 600 mg in adults, based on mg/m^2,. Viloxazine treatment at 82 mg/kg/day during the gestation period caused maternal deaths and decreased body weight in the offspring. The NOAEL for both maternal and developmental toxicity is 33 mg/kg/day, which is less than the MRHD of 600 mg in adults, based on mg/m^2.

8.2 Lactation

Risk Summary

Available data from a lactation study in 15 women indicate that viloxazine and its metabolite, 5-HVLX-gluc, are present in breastmilk. The estimated daily infant dose of viloxazine and 5-HVLX-gluc is 0.085 mg/kg and 0.00595 mg/kg (using a nominal infant body weight of 6 kg), respectively, and the relative infant dose (RID) is approximately 1% and 0.07%, respectively, the weight-normalized maternal daily dose (8.58 mg/kg) of viloxazine. These data support that transfer of viloxazine into breastmilk is low (see Data) . There are no data on the effects of viloxazine on the breastfed infant or the effects on milk production.

The developmental and health benefits of breastfeeding should be considered along with the mother's clinical need for Qelbree and any potential adverse effects on the breastfed child from Qelbree or from the underlying maternal condition.

Data

A multi-dose (600 mg daily for three days) milk and plasma lactation study was conducted in 15 healthy lactating women. The geometric mean of the total excreted amounts of viloxazine and 5-HVLX-gluc in breast milk over a period of 24 hours at steady-state were 0.511 mg and 0.0357 mg, respectively. The RID of viloxazine and 5-HVLX-gluc were approximately 1% and 0.07%, respectively, of the weight-normalized maternal daily dose (8.58 mg/kg) of viloxazine.

8.4 Pediatric Use

The safety and effectiveness of Qelbree in pediatric patients 6 to 17 years of age with ADHD have been established based on randomized, placebo-controlled studies in pediatric patients [see Adverse Reactions (6.1)and Clinical Studies (14)] .

The safety and effectiveness of Qelbree have not been established in pediatric patients younger than 6 years old.

Patients treated with Qelbree should be monitored for suicidal thoughts and behavior [see Warnings and Precautions (5.1)] , and for changes in weight [see Adverse Reactions (6.1)].

Juvenile Animal Toxicity Data

Viloxazine was administered orally to juvenile rats from postnatal day (PND) 23 through PND 79 at doses of 43, 130, and 217 mg/kg/day, which are approximately 1, 2, and 3 times the MRHD of 400 mg in children, based on mg/m^2, respectively. Viloxazine decreased body weight, weight gain, and food consumption in both sexes at 217 mg/kg/day. Sexual maturation, reproductive capacity, and learning and memory were not affected. The NOAEL for juvenile toxicity is 130 mg/kg/day, which is approximately 2 times the MRHD of 400 mg in children, based on mg/m^2.

8.5 Geriatric Use

Clinical trials of Qelbree in the treatment of ADHD did not include sufficient numbers of patients aged 65 and older to determine whether or not they respond differently from younger patients.

8.6 Renal Impairment

Dosage reduction is recommended in patients with severe (eGFR of < 30 mL/min/1.73m^2[MDRD]) renal impairment [see Dosage and Administration (2.4)] .

No dosage adjustment of Qelbree is recommended in patients with mild to moderate (eGFR of 30 to 89 mL/min/1.73m^2[MDRD]) renal impairment.

The exposure of viloxazine increases in patients with renal impairment [see Clinical Pharmacology (12.3)].

10 OVERDOSAGE

Human Experience

The pre-market clinical trials with Qelbree do not provide information regarding symptoms of overdose.

Literature reports from post marketing experience with immediate-release viloxazine include cases of overdosage from 1000 mg to 6500 mg (1.7 to 10.8 times the maximum recommended daily dose). The most reported symptom was drowsiness. Impaired consciousness, diminished reflexes, and increased heart rate have also been reported.

Treatment and Management

There is no specific antidote for Qelbree overdose. Administer symptomatic and supportive treatment as appropriate. In case of overdose, consult a Certified Poison Control Center (1-800-222-1222 or www.poison.org).

11 DESCRIPTION

Qelbree contains viloxazine, a selective norepinephrine reuptake inhibitor, in the form of viloxazine hydrochloride which is (±)-2-[(2-ethoxyphenoxy)methyl]morpholine hydrochloride. The molecular formula is C13H20NO3Cl and its molecular weight is 273.8 (HCl salt) with the following structural formula:

Viloxazine hydrochloride is a white to off-white powder. Viloxazine hydrochloride is soluble in water, 0.1N HCl and aqueous solutions of pH 9.5 and lower. Viloxazine hydrochloride is sparingly soluble in methanol, very slightly soluble in acetonitrile, acetic acid and isopropyl alcohol, and practically insoluble in ethyl acetate.

Qelbree extended-release capsules are intended for oral administration. Each extended-release capsule contains 100 mg, 150 mg, and 200 mg of viloxazine free base equivalent to 115mg, 173mg, and 231mg, respectively, of viloxazine hydrochloride salt.

The inactive ingredients are: Ammonium hydroxide, black iron oxide, butyl alcohol, corn starch, ethylcellulose, FD&C Blue #1, FD&C Red #28, FD&C Yellow #5, FD&C Yellow #6, FD&C Yellow #10, gelatin, hypromellose, isopropyl alcohol, lactose monohydrate, medium chain triglycerides, oleic acid, polyethylene glycol, potassium hydroxide, propylene glycol, shellac, strong ammonia solution, sucrose, talc, triacetin, titanium dioxide.

12 CLINICAL PHARMACOLOGY

12.1 Mechanism of Action

The mechanism of action of viloxazine in the treatment of ADHD is unclear; however, it is thought to be through inhibiting the reuptake of norepinephrine.

12.2 Pharmacodynamics

Viloxazine binds to and inhibits the norepinephrine transporter (Ki=0.13 μM). In addition, viloxazine binds to and exhibits partial agonist activity at the serotonin 5-HT2Creceptor (Ki=0.66 μM).

Cardiac Electrophysiology

At a dose 3 times the maximum recommended dose, Qelbree did not prolong the QT interval to any clinically relevant extent. There was no effect of Qelbree on the PR interval or QRS duration in healthy volunteers. However, nonclinical studies suggest the potential for Qelbree to inhibit cardiac sodium channels.

12.3 Pharmacokinetics

Viloxazine Cmaxand AUC increase proportionally over a dosage range from 100 mg to 600 mg once daily. Steady-state was reached after two days of once-daily administration, and no accumulation was observed.

Absorption

The relative bioavailability of viloxazine extended-release relative to an immediate-release formulation was about 88%. The median (range) time to peak plasma concentration of viloxazine (Tmax) was approximately 5 hours, with a range of 3 to 9 hours, following a single 200 mg dose.

Effect of Food

Administration of 200 mg viloxazine extended-release with a high-fat meal (800 to 1000 calories) decreased viloxazine Cmaxand AUC by about 9% and 8%, respectively. Viloxazine Tmaxincreased by about 2 hours after administration with a high-fat meal. Sprinkling the contents of a capsule on applesauce decreased viloxazine Cmaxand AUC by about 10% and 5%, respectively.

Distribution

Viloxazine is 76-82% bound to human plasma proteins over the blood concentration range of 0.5 mcg/mL to 10 mcg/mL.

Elimination

The mean (± SD) half-life of viloxazine was 7.02 ± (4.74 hours).

Metabolism

Viloxazine is primarily metabolized by CYP2D6, UGT1A9, and UGT2B15. The major metabolite detected in plasma is 5-hydroxy-viloxazine glucuronide.

Excretion

Renal excretion is the primary route of excretion of viloxazine. After administration of radiolabeled viloxazine, 90% of the dose was recovered in urine within the first 24 hours post-dose. Less than 1% of the dose is excreted in the feces.

Specific Populations

Geriatric Patients

No studies were conducted to evaluate pharmacokinetics in the geriatric population.

Pediatric Patients

The estimated steady-state Cmaxand AUC0-tof viloxazine and its major metabolite, at doses ranging from 200 mg to 400 mg, was approximately 130-250% and 60-140% higher in pediatric patients 6 to 11 and 12 to 17 years of age, respectively, compared to adults.

Male or Female Patients and Racial or Ethnic Groups

No clinically significant differences in the pharmacokinetics of viloxazine was observed based on race and sex.

Patients with Hepatic and Renal Impairment

Exposures of viloxazine in patients with hepatic and renal impairment are summarized in Figure 1 [see Dosage and Administration (2.4)and Use in Specific Populations (8.6)]

Figure 1: Effect of Hepatic and Renal Impairment on Viloxazine Pharmacokinetics

CYP2D6 Metabolism

A multiple-dose study was conducted with Qelbree 900 mg once-daily in healthy volunteers to compare the effect of CYP2D6 poor metabolizers (PMs) and extensive metabolizers (EMs) on the PK of viloxazine. At steady state, viloxazine geometric means for Cmaxand AUC0-24were 21% and 26%, respectively, higher in CYP2D6 PMs compared to EMs.

Drug Interaction Studies

Alcohol: There was no significant effect on viloxazine Cmaxand AUC when 200 mg viloxazine ER was administered with orange juice containing 4% and 20% alcohol. However, when administered with orange juice containing 40% alcohol, Cmaxand AUC of viloxazine decreased by about 32% and 19%, respectively. The effect of other drugs on the pharmacokinetics of viloxazine is presented in Figure 2.

Figure 2: Effects of Other Drugs on Viloxazine Pharmacokinetics

The effect of viloxazine on the pharmacokinetics of other drugs is presented in Figure 3 [see Drug Interactions (7.1)] .

Figure 3: Effect of Viloxazine on the Pharmacokinetics of Other Drugs

In Vitro Studies

Based on in vitrodata, drugs that inhibit CYP isozymes, 1A2, 2B6, 2D6, 2C8, 2C9, 2C19, 2E1 and 3A4 are not expected to have significant impact on the pharmacokinetic profile of viloxazine.

Viloxazine does not inhibit CYP2C8, 2C9 or 2C19 activities. Viloxazine is a reversible inhibitor of P450-1A2, 2B6, 2D6 and 3A4/5. Viloxazine is a potential inducer of CYP1A2 and CYP2B6.

Viloxazine is not an inhibitor of P-gp, BCRP, MATE2-K, OATP1B1*1a, and OATP1B3 transporters. Viloxazine appears to be a weak inhibitor of the MATE1. Viloxazine is not a substrate of either OATP1B1*1a or OATP1B3 transporters.

13 NONCLINICAL TOXICOLOGY

13.1 Carcinogenesis, Mutagenesis, and Impairment of Fertility

Carcinogenesis

Viloxazine did not increase the incidence of tumors in rats treated for 2 years at oral doses of 22, 43, and 87 mg/kg/day. The high dose of 87 mg/kg/day is approximately equal to the MRHD of 600 mg in adults, based on mg/m^2.

Viloxazine did not increase the incidence of tumors in Tg.rasH2 mice treated for 26 weeks at oral doses of 4.3, 13, and 43 mg/kg/day.

Mutagenesis

Viloxazine was not genotoxic in a battery of genotoxicity tests. It was not mutagenic in the in vitrobacterial reverse mutation (Ames) assay or clastogenic in the in vitromammalian chromosomal aberration assay or in the in vivorat bone marrow micronucleus assay.

Impairment of Fertility

Viloxazine was orally administered to male and female rats prior to and throughout mating and continued until completion of the second littering at doses of 13, 33, and 82 mg/kg/day. Viloxazine did not affect male or female fertility parameters. The NOAEL for male and female fertility is 82 mg/kg/day, which is approximately equal to the MRHD of 600 mg in adults, based on mg/m^2.

13.2 Animal Toxicology and/or Pharmacology

In animal studies, viloxazine treatment caused dose-dependent convulsions at oral doses of ≥ 130, ≥ 173, and ≥ 39 mg/kg/day in the rat, mouse, and dog, respectively, which are approximately equal to or slightly higher than the MRHD of 600 mg in adults, based on mg/m^2.

14 CLINICAL STUDIES

ADHD Studies in Pediatric Patients

The efficacy of Qelbree in the treatment of ADHD in pediatric patients 6 to 17 years of age was evaluated in three short-term, randomized, placebo-controlled monotherapy trials (Studies 1, 2, and 3).

Study 1 (NCT03247530) was a multicenter, randomized, double-blind, three-arm placebo-controlled, parallel group monotherapy trial in patients 6 to 11 years of age with ADHD. Total duration of treatment was 6 weeks, including a 1-week titration period (starting at 100 mg once daily) and 5-week maintenance phase. Patients were randomized to receive 100 mg, 200 mg, or placebo, given once daily as a single dose. The primary endpoint was the change from baseline to the end of study on the total score on the ADHD Rating Scale (ADHD-RS-5), an 18-question scale that assesses hyperactivity, impulsivity, and inattentive symptoms. Higher ADHD-RS-5 scores reflect more severe symptoms. The Clinical Global Impression-Improvement (CGI-I) score at the end of the study was a secondary endpoint.

A total of 477 patients were randomized in Study 1; 399 completed the study, and 78 discontinued. The change from baseline (reduction) in ADHD-RS-5 total score was statistically significantly greater in patients treated with Qelbree 100 mg or with Qelbree 200 mg than in patients on placebo (see Table 4). Compared with patients on placebo, a statistically significantly greater reduction (improvement) in CGI-I score at the end of the study was observed both in patients treated with Qelbree 100 mg and in patients treated with Qelbree 200 mg.

Study 2 (NCT03247543) was a multicenter, randomized, double-blind, three-arm, placebo-controlled, parallel-group monotherapy trial in patients 6 to 11 years of age with ADHD. Total duration of treatment was 8 weeks, including a 3-week titration period (starting at 100 mg once daily), and a 5-week maintenance phase. Patients were randomized to receive Qelbree 200 mg, Qelbree 400 mg, or placebo, given once daily as a single dose. The primary endpoint was the change from baseline to the end of study on the total score on the ADHD Rating Scale (ADHD-RS-5). The Clinical Global Impression-Improvement (CGI-I) score at the end of the study was a secondary endpoint.

A total of 313 patients were randomized in Study 2; 251 completed the study, and 62 discontinued. The change from baseline (reduction) in ADHD-RS-5 total score was statistically significantly greater in patients treated with Qelbree 200 mg or with Qelbree 400 mg than in patients on placebo (see Table 4). Compared with patients on placebo, a statistically significantly greater reduction (improvement) in CGI-I score at the end of the study was observed both in patients treated with Qelbree 200 mg and in patients treated with Qelbree 400 mg.

Study 3 (NCT03247517) was a multicenter, randomized, double-blind, three-arm, placebo-controlled, parallel-group monotherapy trial in patients 12 to 17 years of age with ADHD. Total duration of treatment was 6 weeks, including 1-week titration period (starting at 200mg once daily) and a 5-week maintenance phase. Patients were randomized to receive Qelbree 200 mg, Qelbree 400 mg, or placebo, given once daily as a single dose. The primary endpoint was the change from baseline to the end of study on the total score on the ADHD Rating Scale (ADHD-RS-5). The Clinical Global Impression-Improvement (CGI-I) score at the end of the study was a secondary endpoint.

A total of 310 patients were randomized in Study 3; 266 completed and 44 discontinued. The change from baseline (reduction) in ADHD-RS-5 total score was statistically significantly greater in patients treated with Qelbree 200 mg or with Qelbree 400 mg than in patients on placebo (see Table 4). Compared with patients on placebo, a statistically significantly greater reduction (improvement) in CGI-I score at the end of the study was observed both in patients treated with Qelbree 200 mg and in patients treated with Qelbree 400 mg.

Table 4. Primary Efficacy Results for Change from Baseline in ADHD-RS-5 Total Score in Pediatric Patients (6 to 17 years) with ADHD (Studies 1, 2, 3)
Study Number (Age range) | Treatment Group | Primary Efficacy Measure: ADHD-RS-5 Total Score
 |  | n | Mean Baseline Score (SD) | LS Mean Change from Baseline (SE) | Placebo-subtracted Difference [Difference (drug minus placebo) in least-squares mean change from baseline] (95% CI)
Study 1 (6 to 11 years) | 100 mg/day [Doses that are statistically significantly superior to placebo after multiplicity adjustment] | 147 | 45.0 (6.53) | -16.6 (1.16) | -5.8 (-8.9, -2.6)
Study 1 (6 to 11 years) | 200 mg/day | 158 | 44.0 (6.80) | -17.7 (1.12) | -6.9 (-10.0, -3.8)
Study 1 (6 to 11 years) | Placebo | 155 | 43.6 (7.05) | -10.9 (1.14) | --
Study 2 (6 to 11 years) | 200 mg/day | 107 | 43.8 (6.54) | -17.6 (1.43) | -6.0 (-10.0, -1.9)
Study 2 (6 to 11 years) | 400 mg/day | 97 | 45.0 (6.55) | -17.5 (1.52) | -5.8 (-9.9, -1.7)
Study 2 (6 to 11 years) | Placebo | 97 | 43.5 (6.79) | -11.7 (1.48) | --
Study 3 (12 to 17 years) | 200 mg/day | 94 | 39.9 (7.22) | -16.0 (1.45) | -4.5 (-8.4, -0.6)
Study 3 (12 to 17 years) | 400 mg/day | 103 | 39.4 (7.59) | -16.5 (1.38) | -5.1 (-8.9, -1.3)
Study 3 (12 to 17 years) | Placebo | 104 | 40.5 (6.79) | -11.4 (1.37) | --
ADHD-RS-5 = Attention-Deficit/Hyperactivity Disorder Rating Scale 5thEdition; n: sample size; SD: standard deviation; SE: standard error; LS Mean: least-squares mean; CI: confidence interval, not adjusted for multiple comparisons

ADHD Study in Adults

The efficacy of Qelbree in the treatment of ADHD in adults 18 to 65 years of age was evaluated in a short-term, randomized, placebo-controlled, flexible-dose monotherapy trial (Study 4).

Study 4 (NCT04016779) was a multicenter, randomized, double-blind, placebo-controlled, flexible-dose, parallel-group monotherapy trial in adults 18 to 65 years of age with ADHD. Total duration of treatment was 6 weeks, starting at 200 mg once daily Week 1 and titrating up 400 mg once daily Week 2. Dose was adjusted by 200 mg per day once a week to a minimum of 200 mg once daily and maximum of 600 mg once daily thereafter. Patients were randomized to receive Qelbree (200 mg to 600 mg), or placebo, given once daily as a single dose. The primary endpoint was the change from baseline to the end of study on the total score on the ADHD Investigator Symptom Rating Scale (AISRS), an 18-item scale corresponding to 18 symptoms of ADHD. Higher AISRS scores reflect more severe symptoms. The change from baseline in the Clinical Global Impression-Severity of Illness (CGI-S) score at the end of the study was the key secondary endpoint.

A total of 374 adult patients were randomized in Study 4; 267 completed and 107 discontinued. The average dose at end of study was 504 mg per day. The change from baseline (reduction) in the AISRS Total score was statistically significantly greater in adults treated with Qelbree than in adults on placebo (see Table 5). In addition, the change from baseline (reduction) in the CGI-S score was statistically significantly greater in adults treated with Qelbree than in adults on placebo.

Table 5. Primary Efficacy Results for Change from Baseline AISRS Total Score in Adults (18 to 60 years of age) with ADHD (Study 4)
Study Number (Population) | Treatment Group | n | Mean Baseline Score (SD) | LS Mean Change from Baseline (SE) | Placebo-subtracted Difference [Difference (drug minus placebo) in least-squares mean change from baseline] (95% CI)
Study 4 (Adults) | Qelbree [Treatment is statistically significantly superior to placebo] (200 mg to 600 mg) | 175 | 38.5 (6.56) | -15.5 (0.91) | -3.7 (-6.2, -1.2)
Study 4 (Adults) | Placebo | 179 | 37.6 (6.62) | -11.7 (0.90) | --
AISRS: Attention-Deficit/Hyperactivity Disorder Investigator Symptom Rating Scale; n: sample size; SD: standard deviation; SE: standard error; LS Mean: least-squares mean; CI: confidence interval, not adjusted for multiple comparisons

16 HOW SUPPLIED/STORAGE AND HANDLING

How Supplied

Qelbree (viloxazine extended-release capsules) are available in the following strengths and colors:

100mg (yellow capsule printed with "SPN" on capsule cap and "100" on capsule body with edible black ink).

- Bottles of 100 capsules………………..…….NDC 17772-131-01
- Bottles of 90 capsules……………………….NDC 17772-131-90
- Bottles of 60 capsules……………………….NDC 17772-131-60
- Bottles of 30 capsules……………………….NDC 17772-131-30

150mg (lavender capsule printed with "SPN" on capsule cap and "150" on capsule body with edible black ink).

- Bottles of 100 capsules………………………NDC 17772-132-01
- Bottles of 90 capsules………………………..NDC 17772-132-90
- Bottles of 60 capsules………………………..NDC 17772-132-60
- Bottles of 30 capsules………………………..NDC 17772-132-30

200mg (light green capsule printed with "SPN" on capsule cap and "200" on capsule body with edible black ink).

- Bottles of 100 capsules…………………..…NDC 17772-133-01
- Bottles of 90 capsules………………………NDC 17772-133-90
- Bottles of 60 capsules………………………NDC 17772-133-60
- Bottles of 30 capsules………………………NDC 17772-133-30

Storage and Handling

Store at 20°C to 25°C (68°F to 77°F); excursions permitted between 15°C to 30°C (59°F to 86°F).

17 PATIENT COUNSELING INFORMATION

Advise the patient to read the FDA-approved patient labeling (Medication Guide).

Suicidal Thoughts and Behaviors

Advise patients and caregivers to monitor for the emergence of suicidal thoughts or behaviors or symptoms that might be precursors to emerging suicidal ideation or behavior, especially early during treatment and when the dosage is adjusted up or down. Instruct patients and caregivers to report such symptoms to the healthcare provider [see Boxed Warningand Warnings and Precautions (5.1)] .

Concomitant Use with Monoamine Oxidase Inhibitors (MAOI)

Caution patients about the concomitant use of Qelbree and monoamine oxidase inhibitors (MAOI), or within 14 days after discontinuing an MAOI, because of an increased risk of hypertensive crisis [see Contraindications (4)and Drug Interactions (7.1)] .

Blood Pressure and Heart Rate Increases

Instruct patients that Qelbree can cause elevations of their blood pressure and pulse rate and they should be monitored for such effects [see Warnings and Precautions (5.2)] .

Activation of Mania/Hypomania

Advise patients and their caregivers to look for signs of activation of mania/hypomania [see Warnings and Precautions (5.3)] .

Somnolence and Fatigue

Advise patients about the potential for somnolence (including sedation and lethargy) and fatigue. Advise patients to use caution when performing activities requiring mental alertness, such as driving a motor vehicle or operating hazardous machinery, until they know how they will be affected by Qelbree [see Warnings and Precautions (5.4)].

Effects on Weight

Advise patients and their caregivers that Qelbree may affect weight and that weight should be monitored while using Qelbree [see Adverse Reactions (6.1)].

Pregnancy

Advise patients that there is a pregnancy registry that monitors pregnancy outcomes in women exposed to Qelbree during pregnancy. Advise females of reproductive potential to inform their healthcare provider of a known or suspected pregnancy to discuss if Qelbree should be discontinued [see Use in Specific Populations (8.1)].

Administration Instructions

Advise patients to take the capsule whole or sprinkled over a teaspoonful or tablespoonful of applesauce or pudding and consume within 15 minutes when mixed with pudding or within 2 hours when mixed with applesauce. Do not cut, chew or crush the capsule [see Dosage and Administration (2.3)] .

Qelbree is manufactured by: Catalent Pharma Solutions, LLC, 1100 Enterprise Drive Winchester, KY 40391.

Distributed by: Supernus Pharmaceuticals, Inc. Rockville, MD 20850 USA

Qelbree is a trademark of Supernus Pharmaceuticals, Inc.

RA-QEL-V3 – 202501

© 2025 Supernus Pharmaceuticals Inc.

MEDICATION GUIDE
QELBREE®(Kel' bree)
(viloxazine extended-release capsules)
for oral use

What is the most important information I should know about QELBREE?
QELBREE can cause serious side effects, including:

- Increased risk of suicidal thoughts or actions.QELBREE may increase suicidal thoughts or actions in children and adults with attention deficit hyperactivity disorder (ADHD), especially within the first few months of treatment or when the dose is changed.
  How can I watch for and try to prevent suicidal thoughts and actions?
  - Pay close attention to any changes, especially sudden changes in mood, behavior, thoughts, or feelings or if you or your child develops suicidal thoughts or actions. This is very important when QELBREE treatment is started or when the dose is changed.
  - Call your healthcare provider right away if you or your child has any new or sudden changes in mood, behavior, thoughts, or feelings, or if you or your child develops suicidal thoughts or actions.
  - Keep all follow-up visits with your healthcare provider as scheduled. Call your healthcare provider between visits as needed, especially if you have concerns about symptoms.
  Call your healthcare provider or get emergency help right away if you or your child has any of the following symptoms, especially if they are new, worse, or worry you:

- attempts to commit suicide
- new or worse depression
- feeling very agitated or restless
- trouble sleeping (insomnia)
- acting aggressive, being angry, or violent
- an extreme increase in activity and talking (mania)

- thoughts about suicide or dying
- new or worse anxiety
- panic attacks
- new or worse irritability
- acting on dangerous impulses
- other unusual changes in behavior or mood

See " What are the possible side effects of QELBREE?" for more information about side effects.

What is QELBREE?
QELBREE is a prescription medicine used to treat attention deficit hyperactivity disorder (ADHD) in adults and children 6 years of age and older.
It is not known if QELBREE is safe and effective in children less than 6 years of age.

Do not take QELBREE if you or your child:

- takes a medicine used to treat depression called a monoamine oxidase inhibitor (MAOI). Ask your healthcare provider or pharmacist if you are not sure if you or your child takes an MAOI.
- stopped taking an MAOI in the last 14 days.
- takes alosetron, duloxetine, ramelteon, tasimelteon, tizanidine, or theophylline.

Before taking QELBREE, tell your healthcare provider about all your or your child's medical conditions, including if you or your child:

- have, or have a family history of, suicide, bipolar disorder, depression, mania or hypomania
- have blood pressure or heart rate problems
- have severe kidney problems. Your healthcare provider may lower the dose of QELBREE.
- are pregnant or plan to become pregnant. QELBREE may cause harm to the mother when taken during pregnancy. You and your healthcare provider will decide if QELBREE should be taken during pregnancy.
  - Tell your healthcare provider right away if you or your child become pregnant or think they are pregnant during treatment with QELBREE.
  - There is a pregnancy registry for females who are exposed to QELBREE during pregnancy. The purpose of the registry is to collect information about the health of females exposed to QELBREE and their baby. If you become pregnant while taking QELBREE, talk to your healthcare provider about registering with the National Pregnancy Registry for Psychiatric Medications by calling 1-866-961-2388 or go to www.womensmentalhealth.org/preg.
- are breastfeeding or plan to breastfeed. QELBREE passes into your breastmilk. Talk to your healthcare provider about the best way to feed the baby during treatment with QELBREE.

Tell your healthcare provider about all the medicines you or your child take,including prescription and over-the-counter medicines, vitamins, and herbal supplements.
QELBREE and other medicines may affect each other causing possible serious side effects.
Your healthcare provider will decide if QELBREE can be taken with other medicines.
Especially tell your healthcare provider if you or your child take:

- MAOIs
- alosetron
- duloxetine
- ramelteon
- tasimelteon
- tizanidine
- theophylline

Know the medicines you or your child takes. Keep a list of them and show it to your healthcare provider and pharmacist when you or your child get a new medicine.
Do not start any new medicine during treatment with QELBREE without first talking to your healthcare provider.

How should I take QELBREE?

- Take QELBREE exactly as your healthcare provider tells you to take it.
- Take QELBREE 1 time each day with or without food.
- Swallow QELBREE capsules whole. Do not cut, crush, or chew the capsules.
- If QELBREE capsules cannot be swallowed whole, the capsule may be opened and the entire contents sprinkled onto a teaspoonful or tablespoonful of pudding or applesauce.
- Swallow all the food mixture right away, without chewing, or within 15 minutes of mixing for pudding, or within 2 hours of mixing for applesauce.
  - Do notchew the food mixture.
  - Do notstore food mixture.
- Talk to your healthcare provider about what you should do if you or your child misses a dose.
- If you or your child take too much QELBREE or overdoses, call your poison control center at 1-800-222-1222 right away, or go to the nearest emergency room.

What should I avoid while taking QELBREE?
Do not drive or operate heavy machinery until you know how QELBREE will affect you. QELBREE may cause you to feel sleepy or tired.

What are the possible side effects of QELBREE?
QELBREE can cause serious side effects, including:

- See " What is the most important information I should know about QELBREE?"
- Increased blood pressure and heart rate.Your healthcare provider should check your or your child's blood pressure and heart rate before starting and during treatment with QELBREE.
- Manic episodes.Manic episodes may happen in people with bipolar disorder who take QELBREE. Symptoms may include:

- greatly increased energy
- racing thoughts
- unusually grand ideas
- talking more or faster than usual

- severe trouble sleeping
- reckless behavior
- excessive happiness or irritability

- Sleepiness and tiredness. See " What should I avoid while taking QELBREE?"

The most common side effects of QELBREE in children 6 to 17 years of age include:

- sleepiness
- tiredness
- vomiting
- irritability

- decreased appetite
- nausea
- trouble sleeping

The most common side effects of QELBREE in adults include:

- insomnia
- sleepiness
- nausea
- dry mouth

- headache
- tiredness
- decreased appetite
- constipation

Effects on weight. Your healthcare provider should check your or your child's weight before starting and during treatment with QELBREE.
These are not all of the possible side effects of QELBREE.
Call your doctor for medical advice about side effects. You may report side effects to FDA at 1-800-FDA-1088.

How should I store QELBREE?

- Store QELBREE capsules at room temperature between 68°F to 77°F (20°C to 25°C).
- Keep QELBREE and all medicines out of the reach of children.

General Information about the safe and effective use of QELBREE.
Medicines are sometimes prescribed for purposes other than those listed in a Medication Guide. Do not take QELBREE for a condition for which it was not prescribed. Do not give QELBREE to other people, even if they have the same symptoms that you have. It may harm them. You can ask your healthcare provider or pharmacist for information about QELBREE that is written for health professionals.

What are the ingredients in QELBREE?
Active ingredient: viloxazine
Inactive ingredients:ammonium hydroxide, black iron oxide, butyl alcohol, corn starch, ethylcellulose, FD&C Blue #1, FD&C Red #28, FD&C Yellow #5, FD&C Yellow #6, FD&C Yellow #10, gelatin, hypromellose, isopropyl alcohol, lactose monohydrate, medium chain triglycerides, oleic acid, polyethylene glycol, potassium hydroxide, propylene glycol, shellac, strong ammonia solution, sucrose, talc, triacetin, titanium dioxide.
Manufactured by: Catalent Pharma Solutions, LLC, 1100 Enterprise Drive, Winchester KY 40391, USA
Distributed by: Supernus Pharmaceuticals, Inc., Rockville, MD USA 20850
© 2025 Supernus Pharmaceuticals Inc.
For more information, go to www.supernus.com or call 1-866-398-0833.
RA-QBE-MGV3-202501

This Medication Guide has been approved by the U.S. Food and Drug Administration.

Revised: 01/2025

PRINCIPAL DISPLAY PANEL - 100 mg Capsule Bottle Label

30 Capsules
NDC 17772-131-30

Qelbree™
(viloxazine
extended-release capsules)

100 mg

Once daily
For oral use

ATTENTION PHARMACIST:
Dispense the Accompanying
Medication Guide to Each Patient

Rx only

PRINCIPAL DISPLAY PANEL - 150 mg Capsule Bottle Label

30 Capsules
NDC 17772-132-30

Qelbree™
(viloxazine
extended-release capsules)

150 mg

Once daily
For oral use

ATTENTION PHARMACIST:
Dispense the Accompanying
Medication Guide to Each Patient

Rx only

PRINCIPAL DISPLAY PANEL - 200 mg Capsule Bottle Label

30 Capsules
NDC 17772-133-30

Qelbree™
(viloxazine
extended-release capsules)

200 mg

Once daily
For oral use

ATTENTION PHARMACIST:
Dispense the Accompanying
Medication Guide to
Each Patient

Rx only